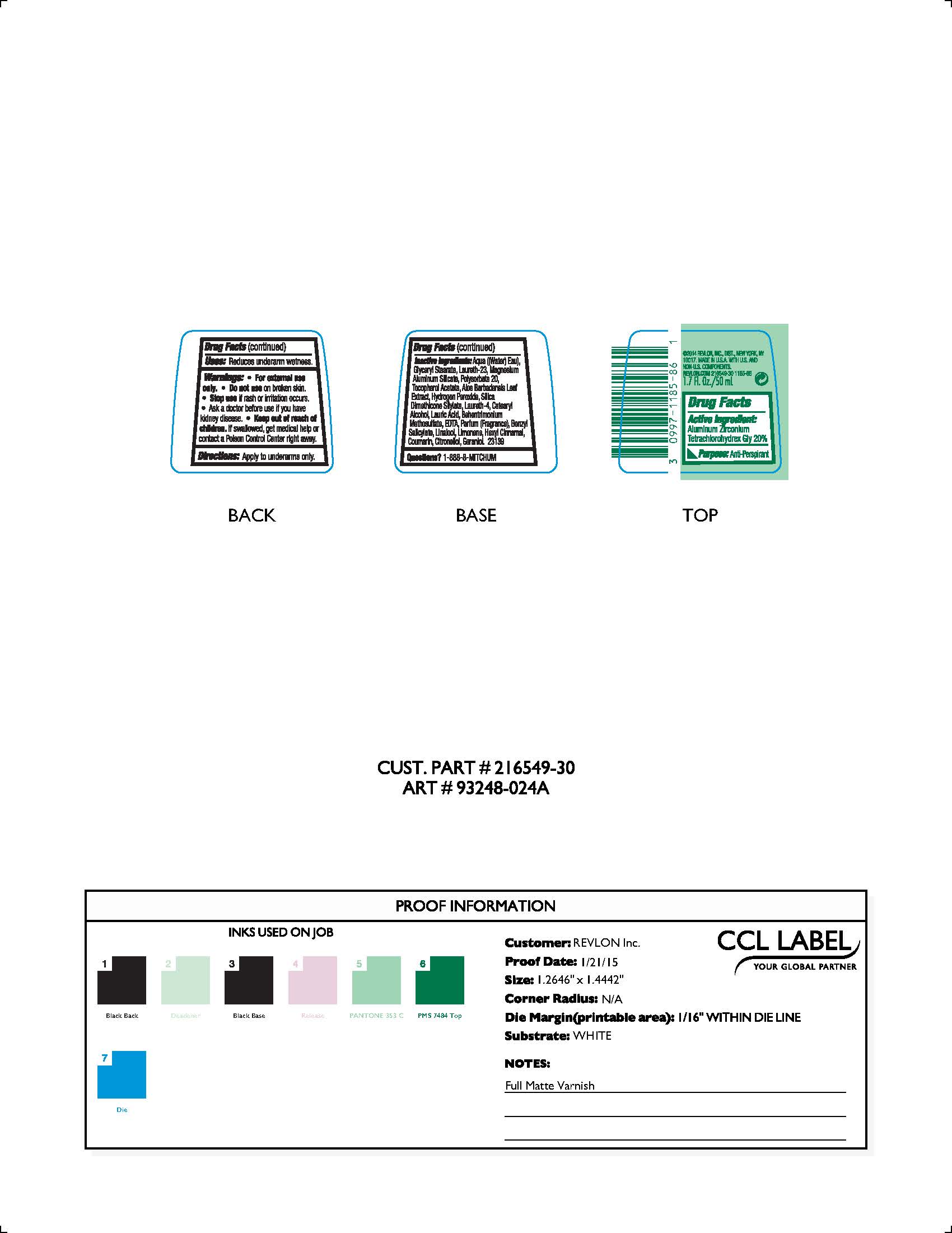 DRUG LABEL: Mitchum Roll On
NDC: 10967-601 | Form: LIQUID
Manufacturer: Revlon Consumer Products Corp
Category: otc | Type: HUMAN OTC DRUG LABEL
Date: 20241231

ACTIVE INGREDIENTS: ALUMINUM ZIRCONIUM TETRACHLOROHYDREX GLY 0.2 g/1 mL
INACTIVE INGREDIENTS: .ALPHA.-TOCOPHEROL ACETATE; WATER; GLYCERYL STEARATE SE; LAURETH-23; MAGNESIUM ALUMINUM SILICATE; POLYSORBATE 20; LAURETH-4; LAURIC ACID; EDETIC ACID; BENZYL SALICYLATE; ALOE VERA LEAF; .BETA.-CITRONELLOL, (R)-; GERANIOL; COUMARIN; HYDROGEN PEROXIDE; LIMONENE, (+/-)-; LINALOOL, (+/-)-

Mitchum Roll-On

ACTIVE INGREDIENT

Aluminum Zirconium Tetrachlorohydrex Gly 20%

Purpose

Antiperspirant

Warnings:

For external use only.

Do not use on broken skin

Ask a doctor before use if you have kidney disease

Stop use if rash or irriation occurs

KEEP OUT OF REACH OF CHILDREN

If swallowed, get medical help or contact a Poison Control Center right away.

Inactive Ingredients

AQUA ((WATER) EAU), GLYCERYL STEARATE, LAURETH-23, MAGNESIUM ALUMINUM SILICATE, POLYSORBATE 20, PARFUM (FRAGRANCE), LAURETH-4, LAURIC ACID, CETEARYL ALCOHOL, EDTA, BENHENTRIMONIUM METHOSULFATE, BENZYL SALICYLATE, LINALOOL, SILICA DIMETHICONE SILYLATE, LIMONENE, HEXYL CINNAMAL, TOCOPHERYL ACETATE, ALOE BARBADENSIS LEAF EXTRACT, COUMARIN, HYDROGEN PEROXIDE, CITRONELLOL, GERANIOL

INDICATIONS AND USAGE

Reduces underarm wetness

PACKAGE LABEL

Mitchum Roll On